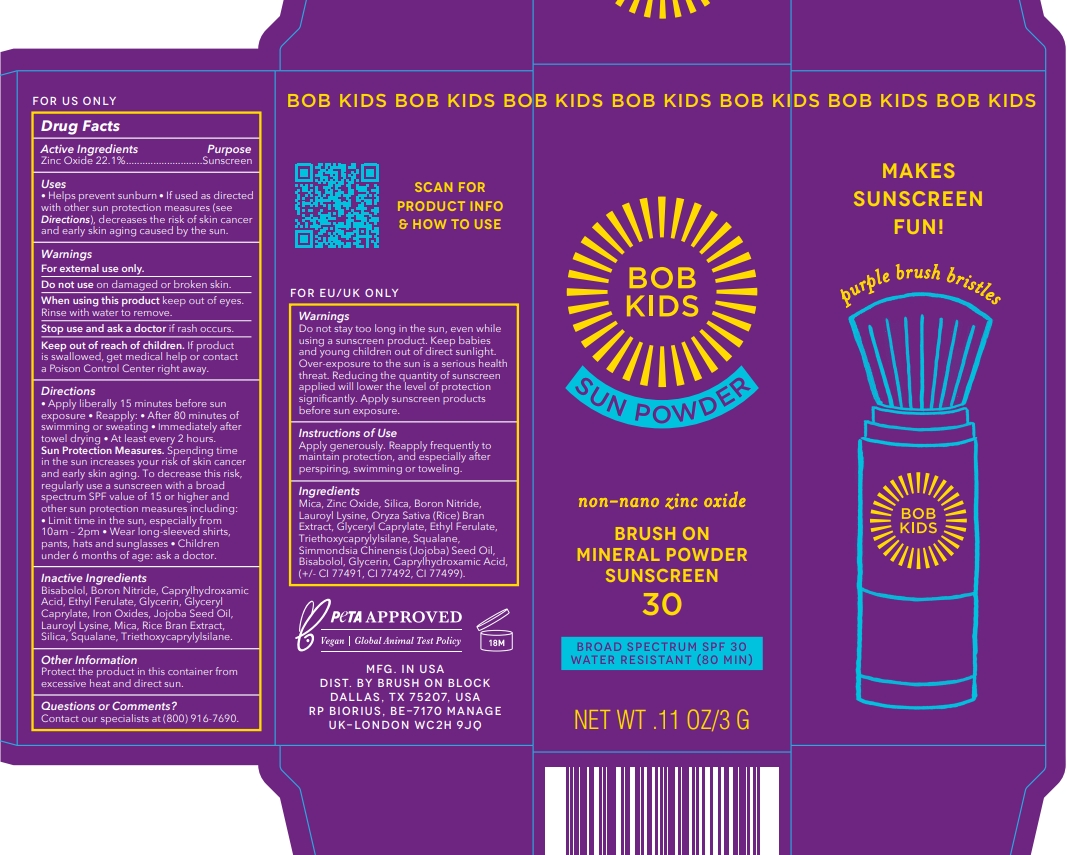 DRUG LABEL: BOB KIDS SPF 30 Zinc only
NDC: 58274-021 | Form: POWDER
Manufacturer: SPF Ventures, LLC
Category: otc | Type: HUMAN OTC DRUG LABEL
Date: 20240612

ACTIVE INGREDIENTS: ZINC OXIDE 22.1 g/100 g
INACTIVE INGREDIENTS: LEVOMENOL; CAPRYLHYDROXAMIC ACID; ETHYL FERULATE; JOJOBA OIL; RICE BRAN; GLYCERYL CAPRYLATE; GLYCERIN; BORON NITRIDE; SQUALANE; TRIETHOXYCAPRYLYLSILANE; MICA; LAUROYL LYSINE; FERRIC OXIDE YELLOW; SILICON DIOXIDE; FERROSOFERRIC OXIDE; FERRIC OXIDE RED

BOB KIDS SPF 30 Zinc only

Active ingredient

Zinc Oxide 22.1%

Purpose

Sunscreen

Uses

- Helps prevent sunburn
- If used as directed with other sun protection measures (see Directions), decreases the risk of skin cancer and early skin aging caused by the sun.

Warnings

For external use only.

Do not use on damaged or broken skin.

When using thi sproduct

When using this product keeo out of eyes. Rinse with water to remove.

Stop use and ask a doctor if rash occurs.

Keep out of reach of children

If product is swallowed, get medical help or contact a Poison Control Center right away.

Directions

- Apply liberally 15 minutes before sun exposure
- Reapply: After 80 minutes of swimming or sweating; Immediately after towel drying; At least every 2 hours
- Sun Proection Measures: Spending time in the sun increases yur risk of skin cancer and early skin aging. To decrease this risk, regularly use a sunscreen with a broad spectrum SPF value of 15 or higher and other sun protection measures including: limit time in the sun, especially from 10am-2pm; Wear long-sleeved shirts, pants, hats and sunglasses; Children under 6 months of age: ask a doctor.

Inactive Ingredients

Mica

Lauroyl lysine

Boron nitride

Silica

Triethoxycaprylylsilane

Ethyl ferulate

Oryza sativa (rice) bran extract

Iron oxides

Bisabolol

Squalane

Simmondsia chinensis (jojoba) seed oil

Glyceryl caprylate

Glycerin

Caprylhydroxamic acid

Other Information

Protect the product in this container from excessive heat and direct sun.